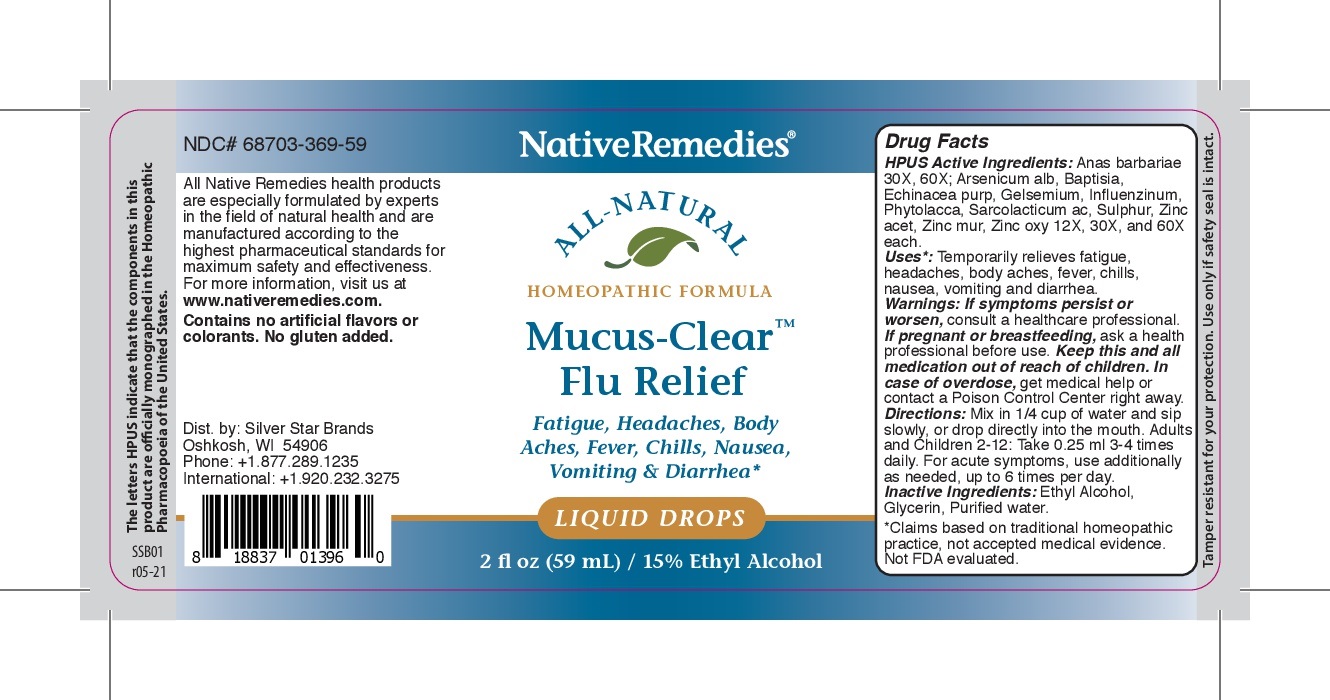 DRUG LABEL: Mucus-Clear Flu Relief
NDC: 68703-369 | Form: LIQUID
Manufacturer: Silver Star Brands
Category: homeopathic | Type: HUMAN OTC DRUG LABEL
Date: 20250101

ACTIVE INGREDIENTS: ARSENIC TRIOXIDE 60 [hp_X]/59 mL; BAPTISIA TINCTORIA 60 [hp_X]/59 mL; ECHINACEA PURPUREA 60 [hp_X]/59 mL; GELSEMIUM SEMPERVIRENS ROOT 60 [hp_X]/59 mL; LACTIC ACID, L- 60 [hp_X]/59 mL; ZINC ACETATE 60 [hp_X]/59 mL; CAIRINA MOSCHATA HEART/LIVER AUTOLYSATE 60 [hp_X]/59 mL; INFLUENZA A VIRUS WHOLE 60 [hp_X]/59 mL; ZINC CHLORIDE 60 [hp_X]/59 mL; INFLUENZA B VIRUS WHOLE 60 [hp_X]/59 mL; PHYTOLACCA AMERICANA ROOT 60 [hp_X]/59 mL; SULFUR 60 [hp_X]/59 mL; ZINC OXIDE 60 [hp_X]/59 mL
INACTIVE INGREDIENTS: GLYCERIN; ALCOHOL; WATER

NativeRemedies® Mucus-Clear™ Flu Relief

HPUS Active Ingredients: Anas barbariae 30X, 60X; Arsenicum alb, Baptisia, Echinacea purp, Gelsemium, Influenzinum, Phytolacca, Sarcolacticum ac, Sulphur, Zinc acet, Zinc mur, Zinc oxy 12X, 30X, and 60X.

Warnings:

Warnings: If symptoms persist or worsen, consult a healthcare professional. If pregnant or breastfeeding, ask a health professional before use. Keep this and all medication out of reach of children. In case of overdose, get medical help or contact a Poison Control Center right away.

Directions:

Directions: Mix in 1/4 cup of water and sip slowly, or drop directly into the mouth. Adults and Children 2-12: Take 0.25 ml 3-4 times daily. For acute symptoms, use additionally as needed, up to 6 times per day.

OTHER SAFETY INFORMATION

Contains no artificial flavors or colorants. No gluten added.

Tamper resistant for your protection. Use only if safety seal is intact.

Inactive Ingredients

Inactive Ingredients: Ethyl alcohol, Glycerin, Purified water.

KEEP OUT OF REACH OF CHILDREN

Keep this and all medication out of reach of children.

PREGNANCY OR BREAST FEEDING

If pregnant or breastfeeding, ask a health care professional before use.

PURPOSE

Fatigue, Headaches, Body Aches, Fever, Chills, Nausea, Vomiting & Diarrhea*

*claims based on traditional homeopathic practice, not accepted medical evidence. Not FDA evaluated.

Uses*:

Uses*: Temporarily relieves fatigue, headaches, body aches, fever, chills nausea, vomiting and diarrhea.

Uses:* Temporarily relieves fatigue, headaches, body aches, fever, chills, nausea, vomiting and diarrhea.

*Claims based on traditional homeopathic practice, not accepted medical evidence. Not FDA evaluated.